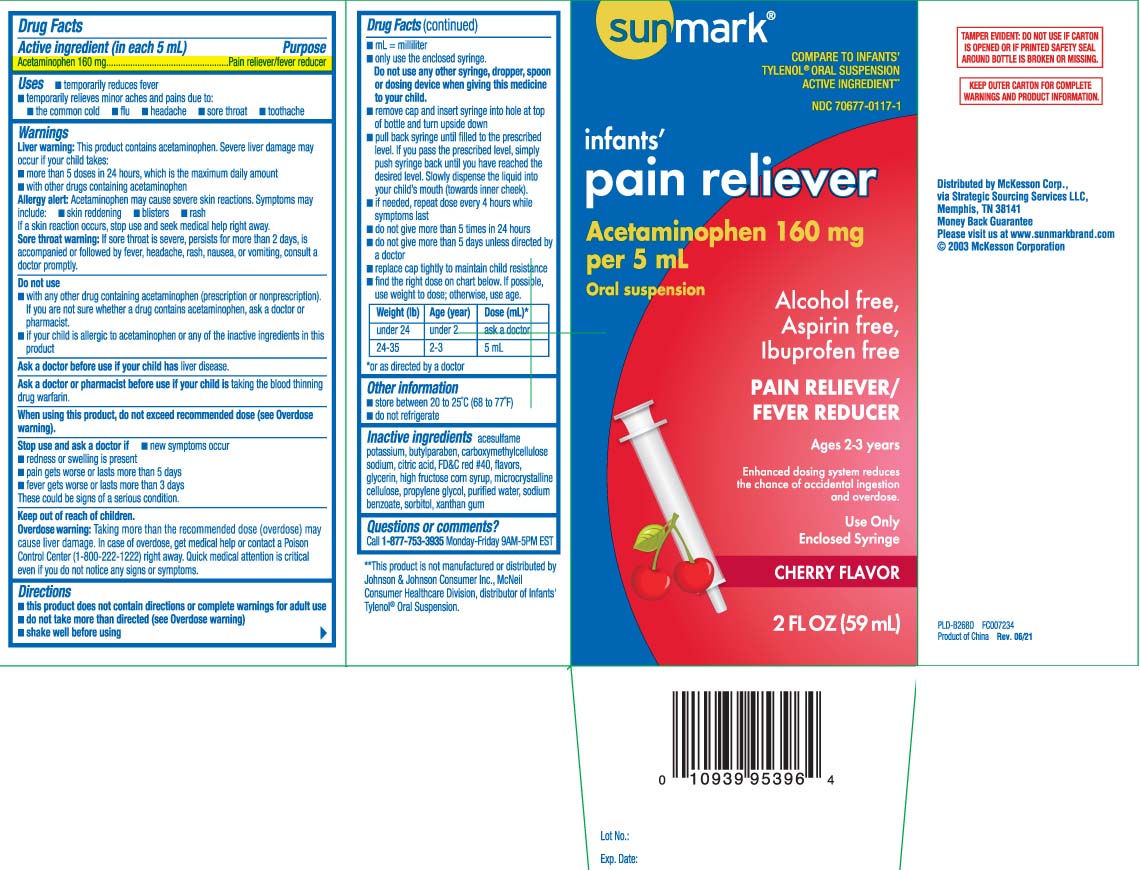 DRUG LABEL: Infants Pain Reliever
NDC: 70677-0117 | Form: SUSPENSION
Manufacturer: Strategic Sourcing Services LLC
Category: otc | Type: HUMAN OTC DRUG LABEL
Date: 20240603

ACTIVE INGREDIENTS: ACETAMINOPHEN 160 mg/5 mL
INACTIVE INGREDIENTS: BUTYLPARABEN; CARBOXYMETHYLCELLULOSE SODIUM; ANHYDROUS CITRIC ACID; FD&C RED NO. 40; GLYCERIN; HIGH FRUCTOSE CORN SYRUP; PROPYLENE GLYCOL; WATER; SODIUM BENZOATE; SORBITOL; XANTHAN GUM; ACESULFAME POTASSIUM; CELLULOSE, MICROCRYSTALLINE

Drug Facts

Active ingredient (in each 5 mL)

Acetaminophen 160 mg

Purpose

Pain reliever/fever reducer

Uses

- temporarily reduces fever
- temporarily relieves minor aches and pains due to
  - the common cold
  - flu
  - headache
  - sore throat
  - toothache

Warnings

Liver warning: This product contains acetaminophen. Severe liver damage may occur if your child takes:

- more than 5 doses in 24 hours, which is the maximum daily amount
- with other drugs containing acetaminophen

Allergy alert: Acetaminophen may cause severe skin reactions. symptoms may include:

- skin reddening
- blisters
- rash

If a skin reaction occurs, stop use and seek medical help right away

Sore throat warning: If sore throat is severe, persists for more than 2 days, is accompanied or followed by fever, headache, rash, nausea, or vomiting, consult a doctor promptly.

Do not use

- with any other drug containing acetaminophen (prescription or non prescription). If you are not sure whether a drug contains acetaminophen, ask a doctor or pharmacist.
- if your child is allergic to acetaminophen or any of the inactive ingredients in this product.

Ask a doctor before use if your child has

liver disease.

Ask a doctor or pharmacist before use if your child is

taking the blood thinning drug warfarin.

When using this product,

do not exceed recommended dose (see overdose warning)

Stop use and ask a doctor if

- new symptoms occur
- redness or swelling is present
- pain gets worse or lasts more than 5 days
- fever gets worse or lasts more than 3 days

These could be signs of a serious condition.

Keep out of reach of children.

Overdose warning: Taking more than the recommended dose (overdose) may cause liver damage. In case of overdose, get medical help or contact a Poison Control Center (1-800-222-1222) right away. Quick medical attention is critical even if you do not notice any signs or symptoms.

Directions

- this product does not contain directions or complete warnings for adult use.
- do not take more than directed (see overdose warning)
- shake well before using
- mL= milliliter
- only use the enclosed syringe. Do not use any other syringe, dropper, spoon or dosing device when giving this medicine to your child
- remove cap, insert syringe into hole at top of bottle and turn upside down
- pull back syringe until filled to be prescribed level. If you pass the prescribed level, invert assembly to right side up on flat surface and simply push syringe back until you have reached the desired level. Slowly dispense the liquid into your child's mouth (towards inner cheek)
- If needed, repeat dose every 4 hours while syptoms last
- do not give more than 5 times in 24 hours
- do not give more than 5 days unless directed by a doctor
- replace cap tightly to maintain child resistance
- find the right dose on chart below. If possible, use weight to dose; otherwise, use age

Weight (lb) | Age (year) | Dose (mL)*
under 24 | under 2 years | ask a doctor
24-35 | 2-3 years | 5 mL

*or as directed by a doctor

Other information

- store between 20-25ºC (68º-77ºF)
- do not refrigerate.
- see bottom panel for lot number and expiration date

Inactive ingredients

acesulfame potassium, butylparaben, carboxymethylcellulose sodium, citric acid, FD&C red #40, flavors, glycerin, high fructos corn syrup, microcrystalline cellulose, propylene glycol, purfied water, sodium benzoate, sorbitol, xanthan gum

Questions or comments?

Call 1-877-753-3935 Monday-Friday 9AM-5PM EST

Principal Display Panel

COMPARE TO INFANTS' TYLENOL® ORAL SUSPENSION ACTIVE INGREDIENT**

Infants' Pain Reliever

Acetaminophen 160 mg per 5 mL

Oral suspension alcohol free

- aspirin free
- alcohol free
- ibuprofen free

PAIN RELIEVER / FEVER REDUCER

Ages 2-3 years

Enhanced dosing system reduces the chance of accidental ingestion and overdose

Use Only Enclosed Syringe

CHERRY FLAVOR

fl oz (mL)

**This product is not manufactured or distributed by Johnson & Johnson Consumer Inc., McNeil Consumer Healthcare Division, distributor of Infants' Tylenol® Oral Suspension.

TAMPER EVIDENT: DO NOT USE IF CARTON IS OPENED OR IF PRINTED SAFETY SEAL AROUND BOTTLE IS BROKEN OR MISSING.

KEEP OUTER CARTON FOR COMPLETE WARNINGS AND PRODUCT INFORMATION.

Distributed by McKesson Corp.,

via Strategic Sourcing Services LLC,

Memphis, TN 38141

www.sunmarkbrand.com

Package Label

SUNMARK Infants' Pain Reliever